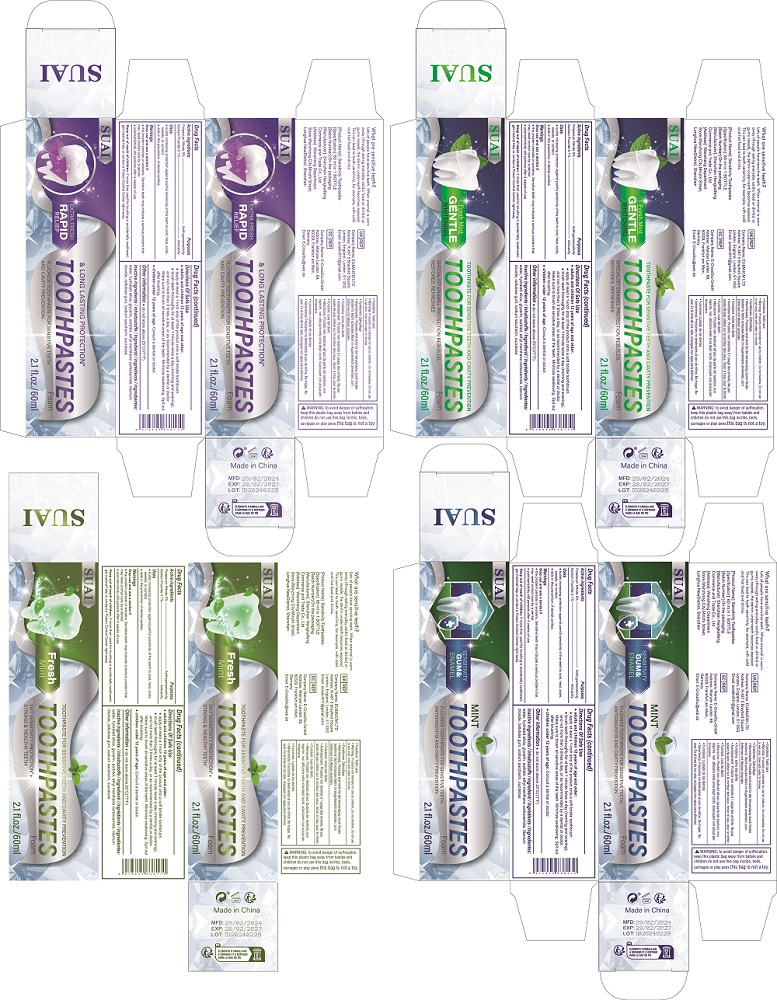 DRUG LABEL: Sensitivity Toothpastes
NDC: 84117-013 | Form: LIQUID
Manufacturer: Shenzhen Hengkaifeng Commerce and Trade Co., Ltd
Category: otc | Type: HUMAN OTC DRUG LABEL
Date: 20240703

ACTIVE INGREDIENTS: HYDRATED SILICA 5 g/100 mL
INACTIVE INGREDIENTS: WATER

ACTIVE INGREDIENT

Potassium Nitrate 5%
Sodium Fluoride 0.1%

Purpose

Antihypersensitivity
Anticavity

Use

● builds increasing protection against painful sensitivity of the teeth to cold, heat, acids,
sweets, or contact.
● alds in the prevention cf dental cavities.

Warnings

Stop use and ask a dentist if
● the problem persists or worsens. Sensitive teeth may indicate a serious problem that
may need prompt care by a dentist.
● pain/sensitivity still persists after 4 weeks of use.

Keep out of reach of children. if more than used for brushing is accidentally swallowed,
get medical help or contact a Poison Control Center right away.

Directions Of Safe Use

● adults and children 12 years of age and older:
● apply at least a 1-inch strip of the product onto a soft bristle toothbrush.
● brush teeth thoroughly for at least 1 minute twice a day (morning and evening),
and not more than 3 times a day, or as recommended by a dentist or doctor.
Make sure to brush all sensitive areas of the teeth. Minimize swallowing. Spit out
after brushing.
● children under 12 years of age: Consult a dentist or doctor.

Inactive ingredients

water, hydrated silica, glycerin, sorbitol, ethyl menthane carboxamide, titanium
dioxide, cellulose gum, sodium saccharin, sucralose

DOSAGE AND ADMINISTRATION

apply at least a 1-inch strip of the product onto a soft bristle toothbrush.